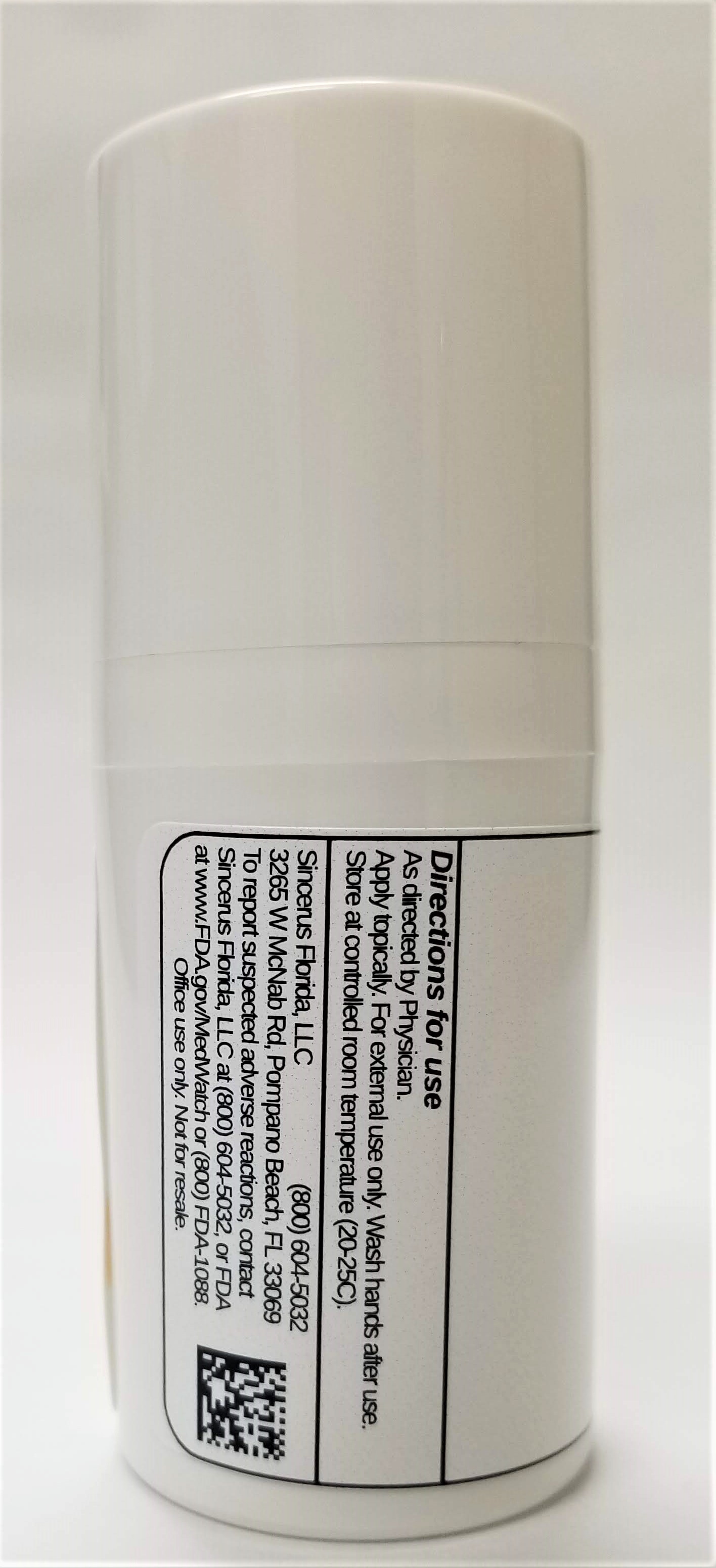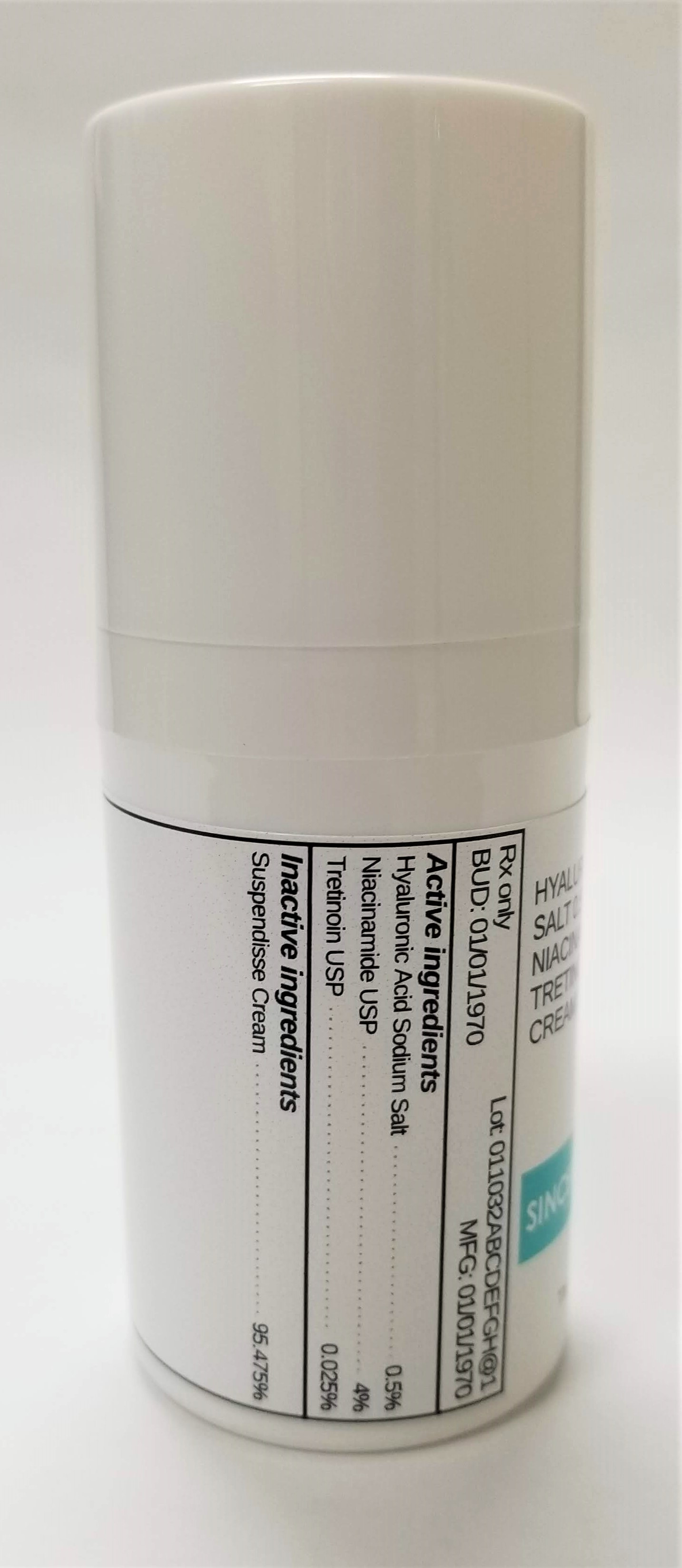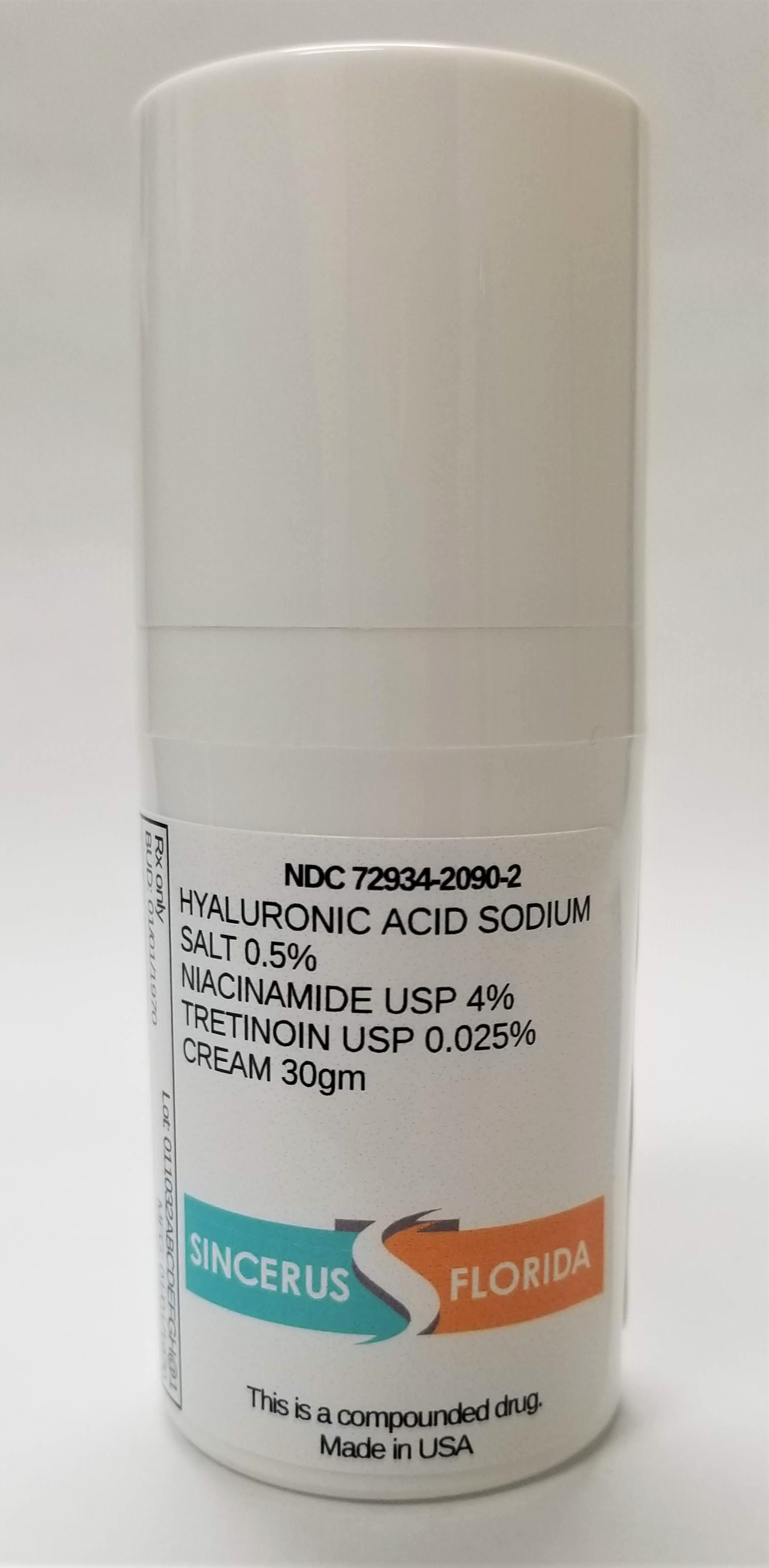 DRUG LABEL: HYALURONIC ACID SODIUM SALT 0.5% / NIACINAMIDE 4% / TRETINOIN 0.025%
NDC: 72934-2090 | Form: CREAM
Manufacturer: Sincerus Florida, LLC
Category: prescription | Type: HUMAN PRESCRIPTION DRUG LABEL
Date: 20190423

ACTIVE INGREDIENTS: HYALURONIC ACID 0.5 g/100 g; NIACINAMIDE 4 g/100 g; TRETINOIN 0.025 g/100 g

HYALURONIC ACID SODIUM SALT 0.5% / NIACINAMIDE 4% / TRETINOIN 0.025%